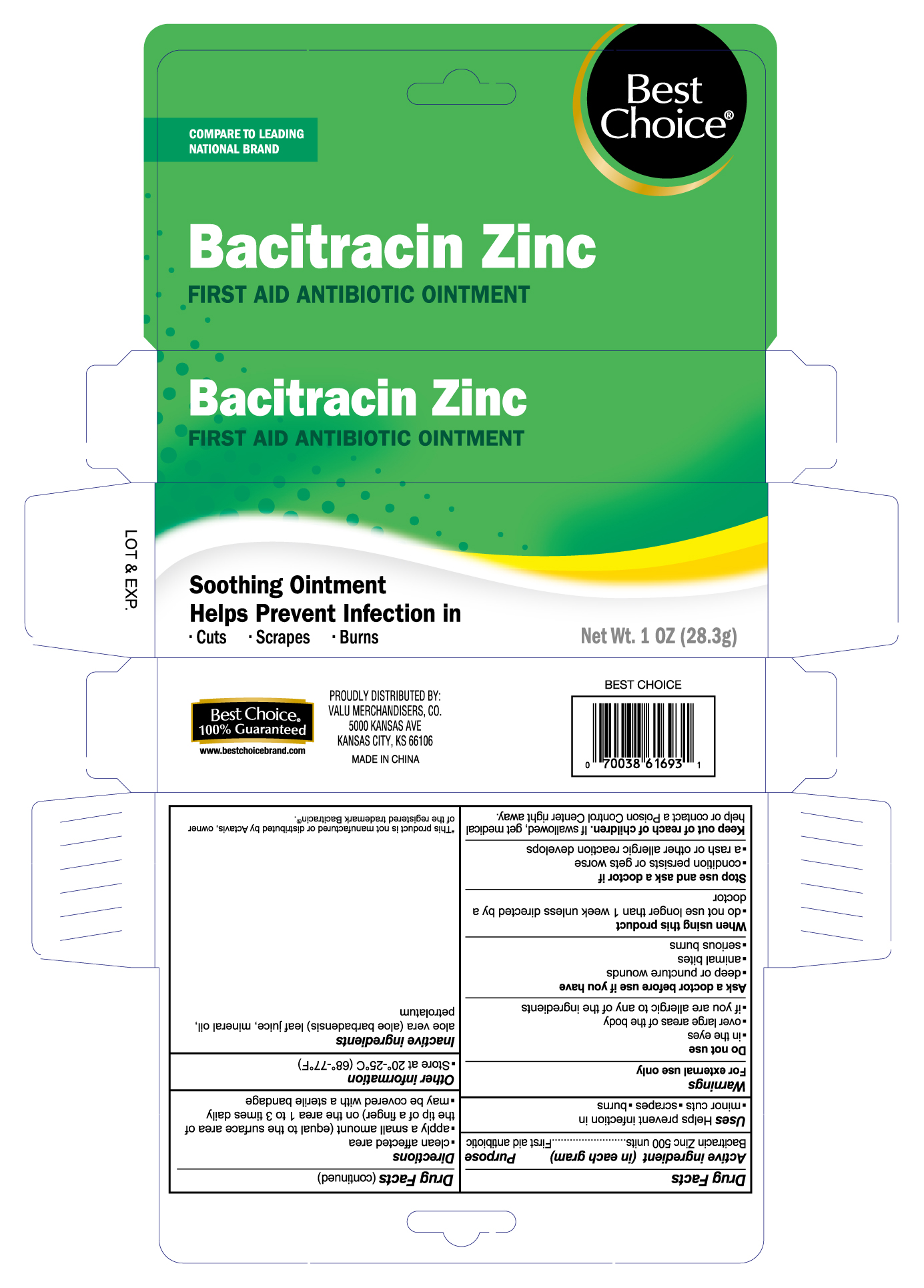 DRUG LABEL: Best Choice Bacitracin Zinc
NDC: 63941-616 | Form: OINTMENT
Manufacturer: Valu Merchandisers, Co.
Category: otc | Type: HUMAN OTC DRUG LABEL
Date: 20230208

ACTIVE INGREDIENTS: BACITRACIN ZINC 500 [USP'U]/1 g
INACTIVE INGREDIENTS: MINERAL OIL; PETROLATUM; ALOE VERA LEAF

Best Choice Bacitracin

Active ingredient (in each gram)

Bacitracin Zinc 500 units

Purpose

First aid antibiotic

Uses

first aid to help prevent infection in minor cuts, scrapes and burns

Warnings

For external use only

Do not use

- in the eyes
- over large areas of the body
- if you are allergic to any of the ingredients
- longer than 1 week unless directed by a doctor

Ask a doctor before use if you have

in case of deep or puncture wounds, animal bites or serious burns

Stop use and ask a doctor if

- condition persists or gets worse
- rash or other allergic reaction develops

Keep out of reach of children

If swallowed, get medical help or contact a Poison Control Center right away.

Directions

- clean the affected area
- apply a small amount of this product (an amount equal to the surface area of the tip of a finger) on the area 1 to 3 times daily
- may be covered with a sterile bandage

Other information

store at room temperature

Inactive ingredients

aloe vera (aloe barbadensis) leaf juice, mineral oil, petrolatum

Package label

Best Choice Bacitracin Zinc